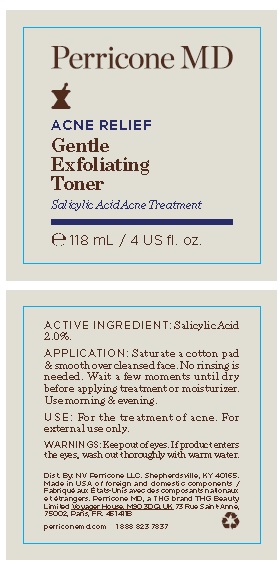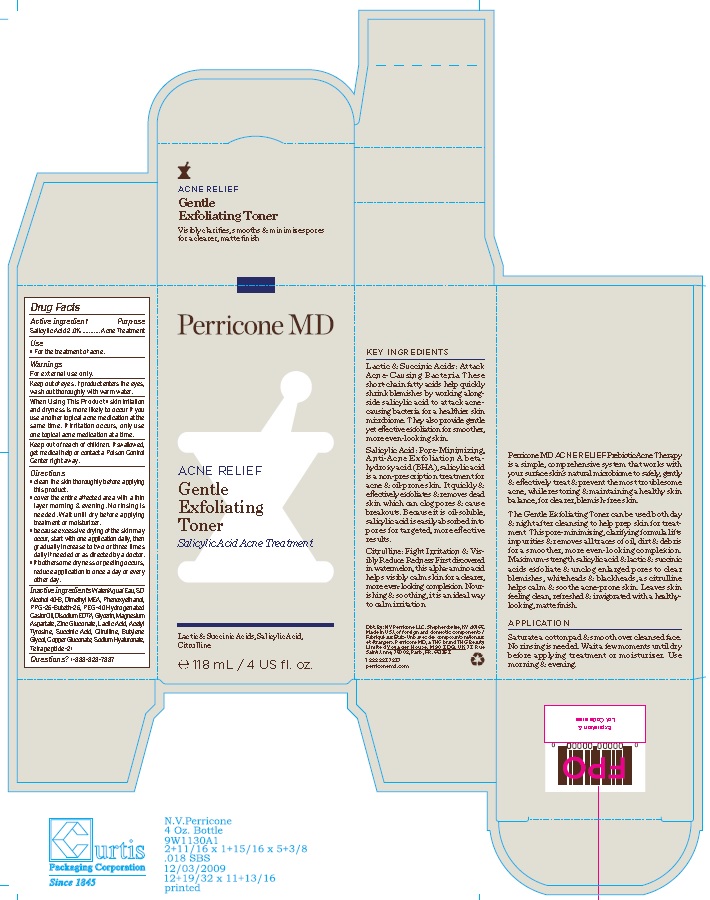 DRUG LABEL: Perricone Acne Relief Gentle Exfoliating Toner
NDC: 54111-157 | Form: SOLUTION
Manufacturer: Bentley Laboratories, LLC
Category: otc | Type: HUMAN OTC DRUG LABEL
Date: 20210911

ACTIVE INGREDIENTS: SALICYLIC ACID 2.0 g/100 mL
INACTIVE INGREDIENTS: WATER; ALCOHOL; DEANOL; PHENOXYETHANOL; PPG-26-BUTETH-26; POLYOXYL 40 HYDROGENATED CASTOR OIL; EDETATE DISODIUM ANHYDROUS; GLYCERIN; MAGNESIUM ASPARTATE; ZINC GLUCONATE; LACTIC ACID; ACETYL L-TYROSINE; SUCCINIC ACID; CITRULLINE; BUTYLENE GLYCOL; COPPER GLUCONATE; HYALURONATE SODIUM; TETRAPEPTIDE-21

Perricone MD Acne Relief Gentle Exfoliating Toner

Drug Facts

Active Ingredient

Salicylic Acid (2.0%)

Purpose
Acne Treatment

INDICATIONS AND USAGE

Use ■ For the treatment of acne.

Warnings
For external use only.

Keep out of eyes. If product enters the eyes,
wash out thoroughly with warm water.

When Using This Product ■ skin irritation
and dryness is more likely to occur if you
use another topical acne medication at the
same time. If irritation occurs, only use
one topical acne medication at a time.

Keep out of reach of children. If swallowed,
get medical help or contact a Poison Control
Center right away.

Directions
■ clean the skin thoroughly before applying
this product.
■ cover the entire affected area with a thin
layer morning & evening. No rinsing is
needed. Wait until dry before applying
treatment or moisturizer.
■ because excessive drying of the skin may
occur, start with one application daily, then
gradually increase to two or three times
daily if needed or as directed by a doctor.
■ if bothersome dryness or peeling occurs,
reduce application to once a day or every
other day.

Inactive ingredients Water/Aqua/Eau, SD
Alcohol 40-B, Dimethyl MEA, Phenoxyethanol,
PPG-26-Buteth-26, PEG-40 Hydrogenated
Castor Oil, Disodium EDTA, Glycerin, Magnesium
Aspartate, Zinc Gluconate, Lactic Acid, Acetyl
Tyrosine, Succinic Acid, Citrulline, Butylene
Glycol, Copper Gluconate, Sodium Hyaluronate,
Tetrapeptide-21

Questions?1-888-823-7837

Product Label

Perricone MD

ACNE RELIEF

Gentle
Exfoliating
Toner
Salicylic Acid Acne Treatment

Lactic & Succinic Acids, Salicylic Acid,
Citrulline

℮ 118 mL / 4 US fl. oz.

Dist. By: NV Perricone LLC. Shepherdsville, KY
40165. Made in USA of foreign and domestic
components. Perricone MD, a THG brand THG
Beauty Limited Voyager House, M90 3DQ, UK
73 Rue Saint-Anne, 75002, Paris, FR. 651362

1 888 823 7837
perriconemd.com

res